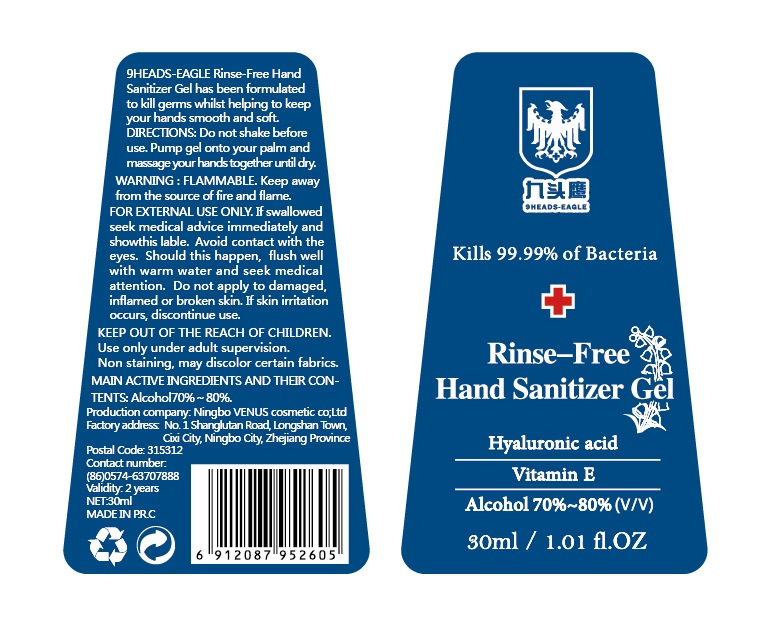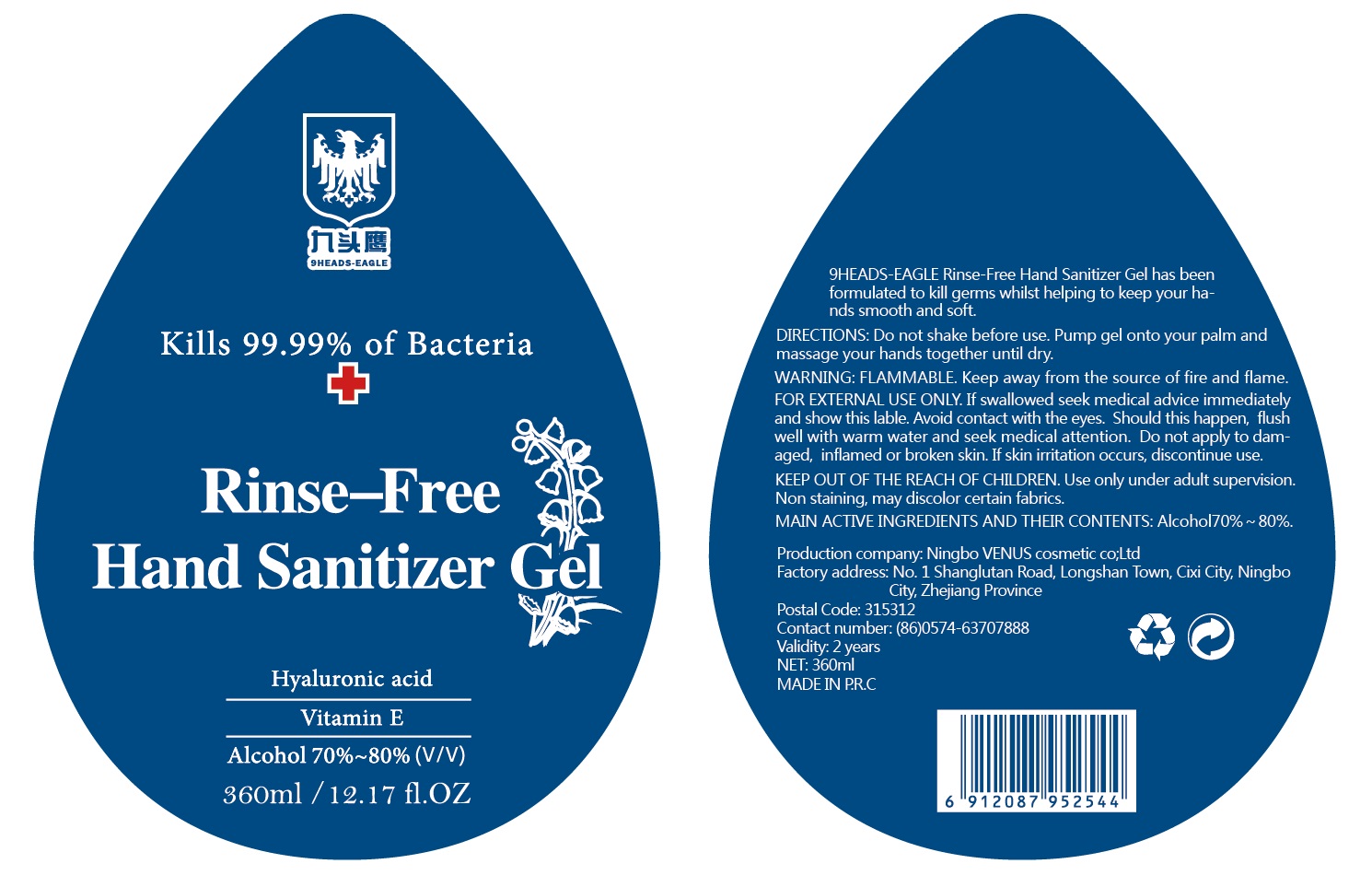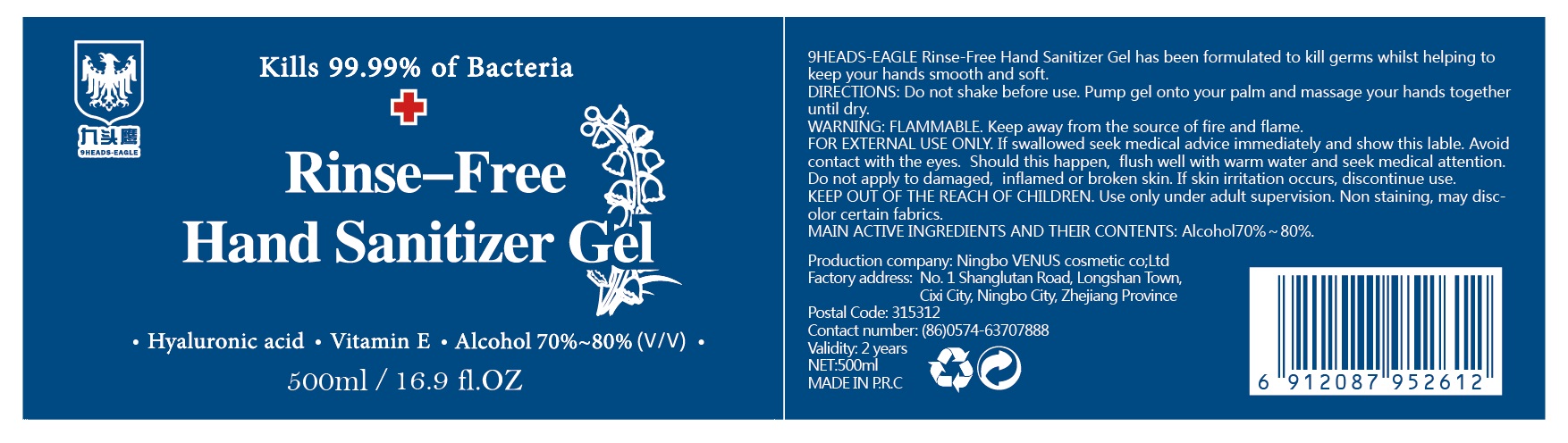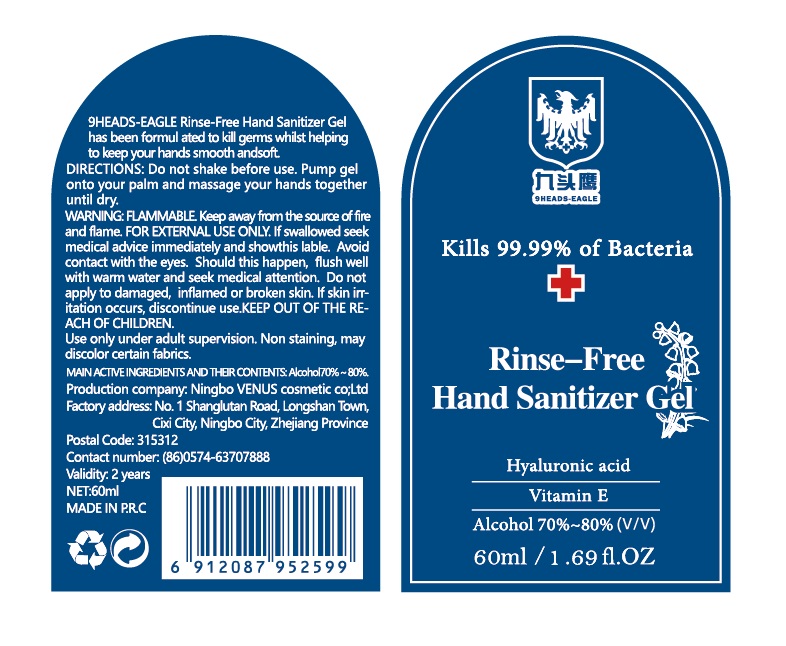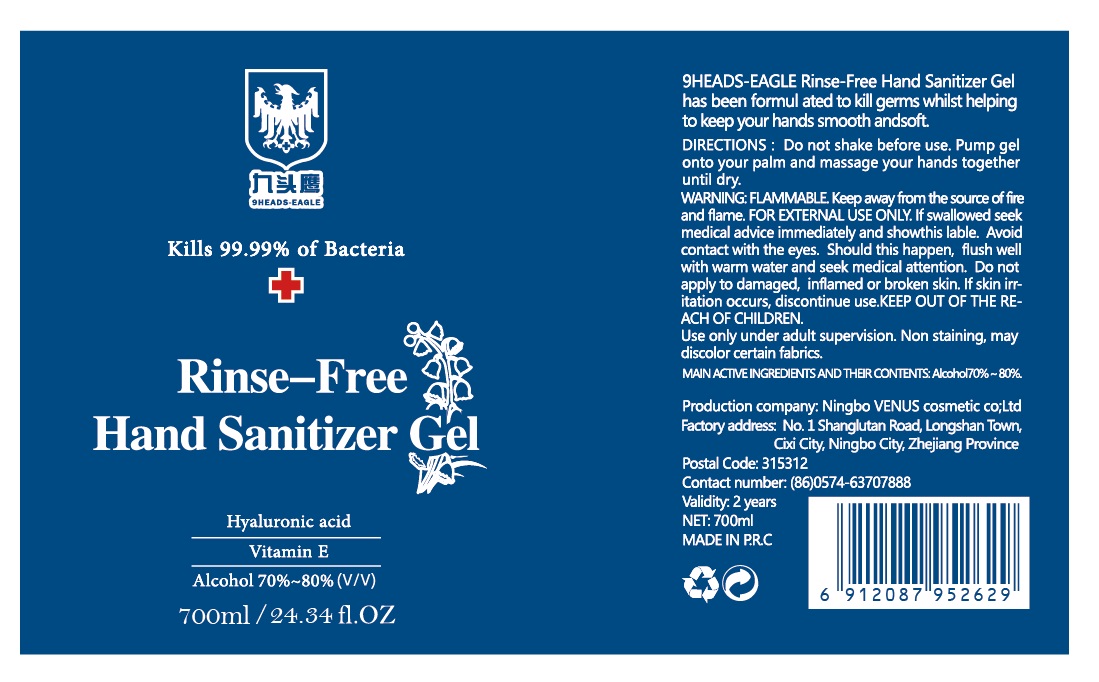 DRUG LABEL: Rinse-Free Hand Sanitizer
NDC: 14341-005 | Form: SPRAY
Manufacturer: Ningbo Venus Cosmetic Co., Ltd.
Category: otc | Type: HUMAN OTC DRUG LABEL
Date: 20201119

ACTIVE INGREDIENTS: ALCOHOL 80 mL/100 mL
INACTIVE INGREDIENTS: GLYCERIN 1.45 mL/100 mL; HYDROGEN PEROXIDE 0.125 mL/100 mL; WATER

14341-005
Rinse-Free Hand Sanitizer

Active Ingredient(s)

Alcohol 80% v/v. Purpose: Antiseptic

Purpose

9HEADS-EAGLE Rinse-free Hand Sanitizer Gel has been formul ated to kill germs whilst helping to keep your hands smooth and soft.

DIRECTIONS

Do not shake before use. Pump gel onto your palm and massage your hands together until dry

Warnings

FLAMMABLE. Keep away from the source of fire and flame FOR EXTERNAL USE ONLY.

Do not use

- in children less than 2 months of age
- on open skin wounds

When using this product keep out of eyes, ears, and mouth. In case of contact with eyes, rinse eyes thoroughly with water.
Stop use and ask a doctor if irritation or rash occurs. These may be signs of a serious condition.
Keep out of reach of children. If swallowed, get medical help or contact a Poison Control Center right away.

If skin irritation occurs, discontinue use.

Keep out of reach of children. If swallowed, get medical help or contact a Poison Control Center right away.

Directions

- Place enough product on hands to cover all surfaces. Rub hands together until dry.
- Supervise children under 6 years of age when using this product to avoid swallowing.

Other information

- Store between 15-30C (59-86F)
- Avoid freezing and excessive heat above 40C (104F)
- Non staining, may discolor certain fabrics.

Inactive ingredients

glycerin, hydrogen peroxide, purified water USP